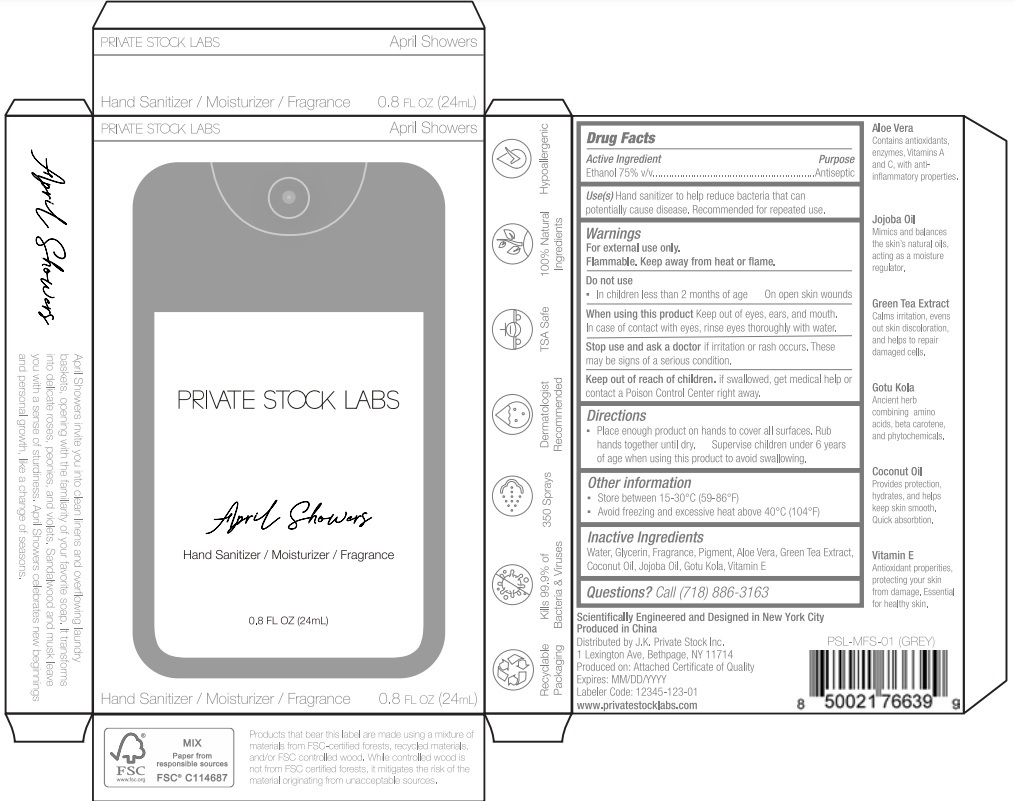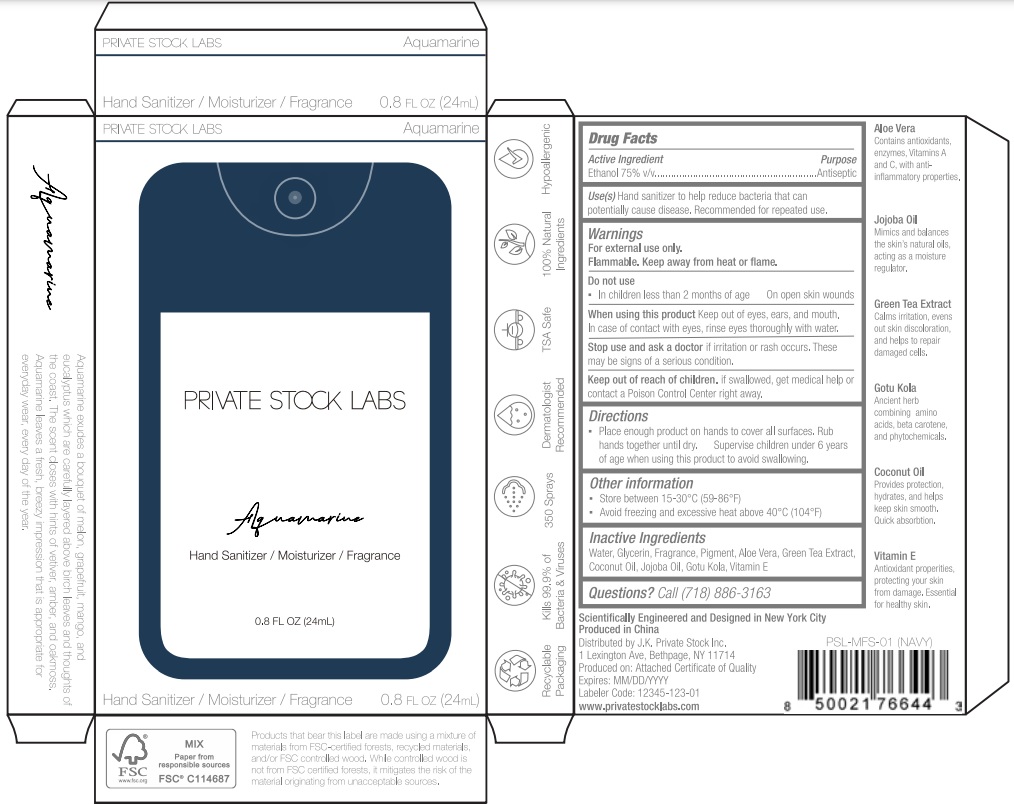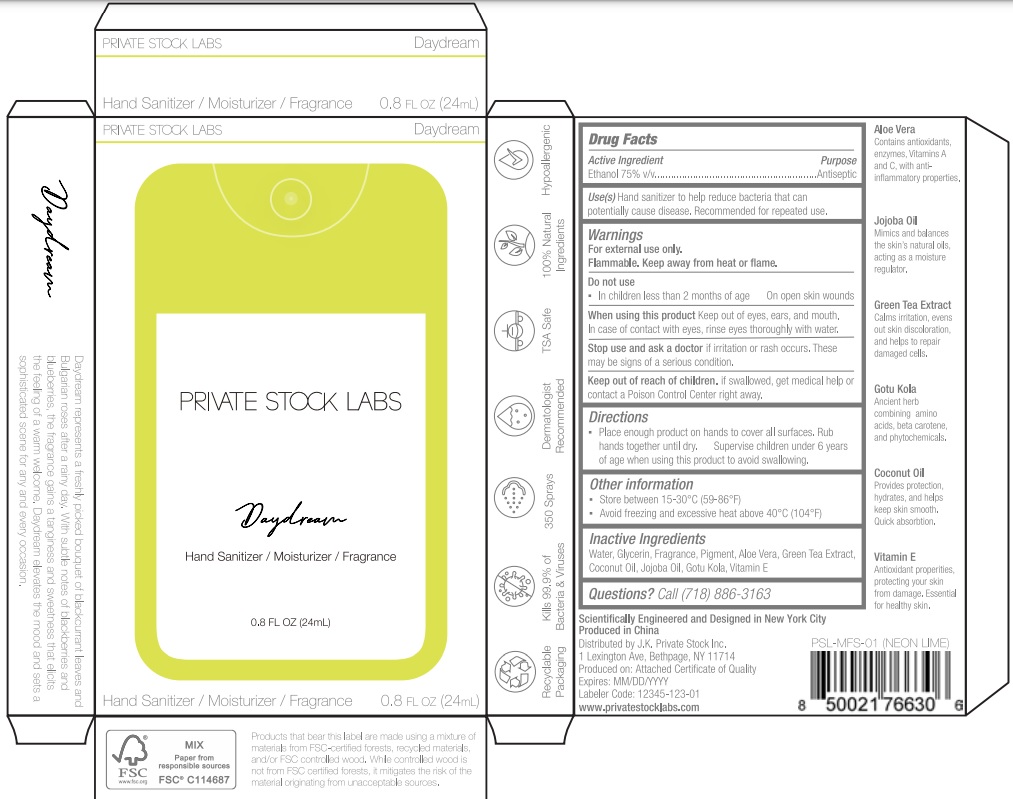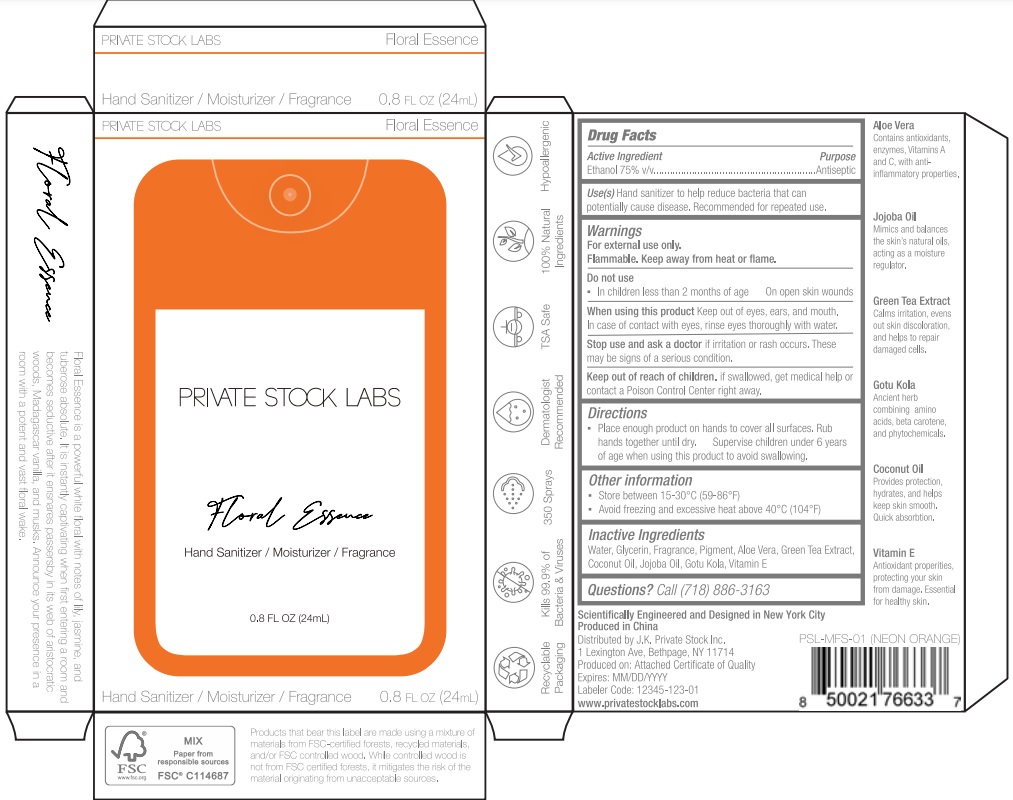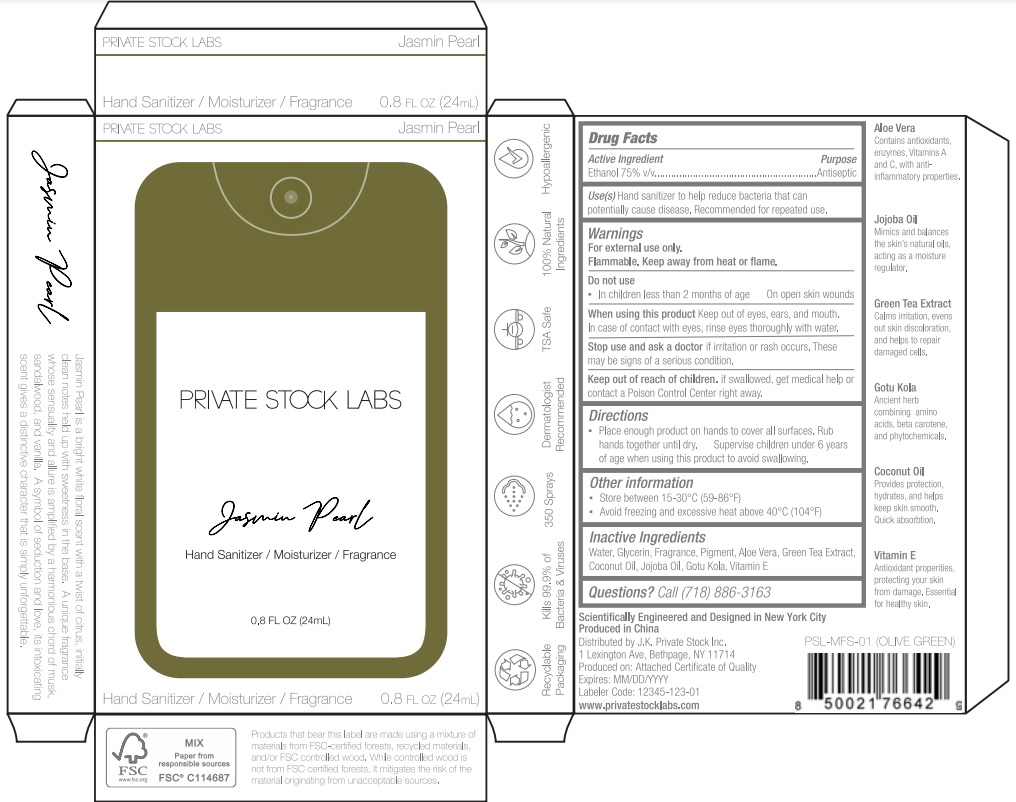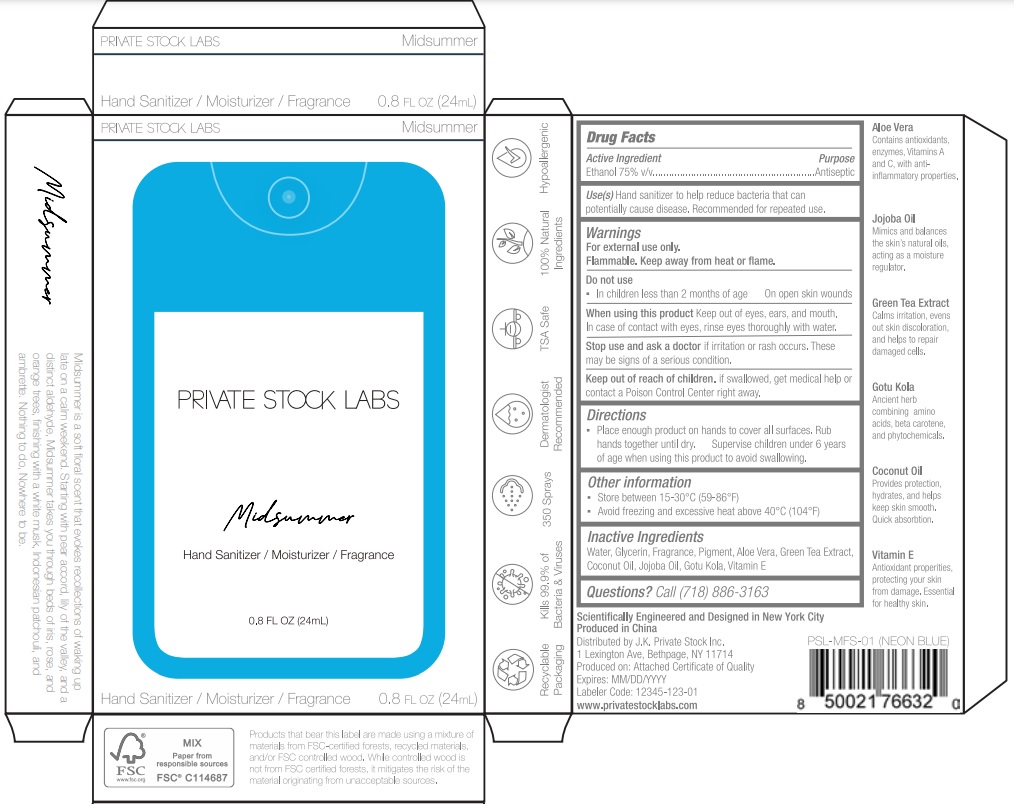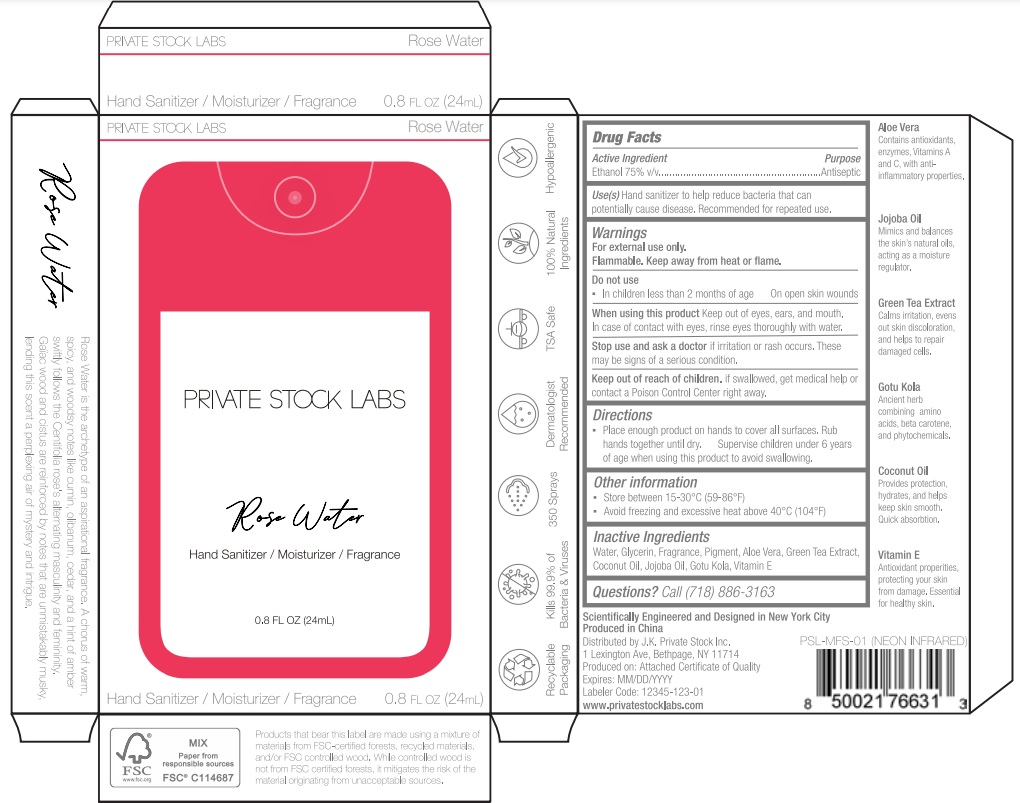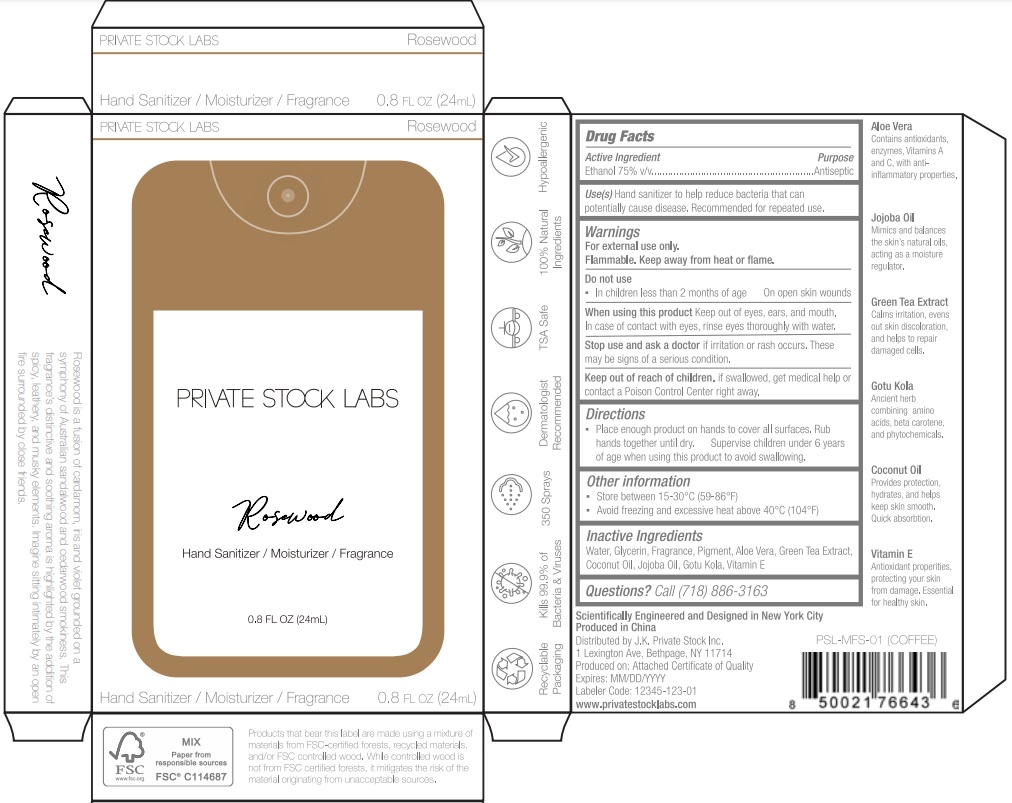 DRUG LABEL: Hand Sanitizer
NDC: 82999-001 | Form: GEL
Manufacturer: J.K. Private Stock Inc
Category: otc | Type: HUMAN OTC DRUG LABEL
Date: 20221114

ACTIVE INGREDIENTS: ALCOHOL 75 mL/100 mL
INACTIVE INGREDIENTS: CENTELLA ASIATICA LEAF; WATER; .ALPHA.-TOCOPHEROL; GLYCERIN; ALOE VERA WHOLE; GREEN TEA LEAF; COCONUT OIL; JOJOBA OIL

Hand Sanitizer -

Active ingredient

Ethanol 75% v/v

Purpose

Antiseptic

Use(s)

Hand sanitizer to help reduce bacteria that can potentially cause disease. Recommended for repeated use.

Warnings

For external use only.

Flammable. Keep away from heat or flame.

Do not use

- In children less than 2 months of age
- On open skin wounds

When usiing this product

Keep out of eyes, ears, and mouth. In case of contact with eyes, rinse eyes throughly with water.

Stop use and ask a doctor

if irritation or rash occurs. These may be signs of a serious condition.

Keep out out reach of children.

if swallowed, get medical help or contact a Poison Control Center right away.

Directions

- Place enough product on hands to cover all surfaces. Rub hands together until dry. Supervise children under 6 years of age when using this product to avoid swallowing.

Other information

- Store between 15-30ºC (59-86ºF)
- Avoid freezing and excessive heat above 40ºC (104ºF)

Inactive Ingredients

Water, Glycerin, Fragrance, Pigment, Aloe Vera, Green Tea Extract, Coconut Oil, Jojoba Oil, Gotu Kola, Vitamin E

Questions?

Call (718) 886-3163

Principal Display

PRIVATE STOCK LABS

April Showers

Hand Sanitizer / Moisturizer / Fragrance

0.8 FL OZ (24mL)

82999-001-01

PRIVATE STOCK LABS

Aquamarine

Hand Sanitizer / Moisturizer / Fragrance

0.8 FL OZ (24mL)

82999-001-02

PRIVATE STOCK LABS

Daydream

Hand Sanitizer / Moisturizer / Fragrance

0.8 FL OZ (24mL)

82999-001-03

PRIVATE STOCK LABS

Floral Essence

Hand Sanitizer / Moisturizer / Fragrance

0.8 FL OZ (24mL)

82999-001-04

PRIVATE STOCK LABS

Jasmin Pearl

Hand Sanitizer / Moisturizer / Fragrance

0.8 FL OZ (24mL)

82999-001-05

PRIVATE STOCK LABS

Midsummer

Hand Sanitizer / Moisturizer / Fragrance

0.8 FL OZ (24mL)

82999-001-06

PRIVATE STOCK LABS

Rose Water

Hand Sanitizer / Moisturizer / Fragrance

0.8 FL OZ (24mL)

82999-001-07

PRIVATE STOCK LABS

Rosewood

Hand Sanitizer / Moisturizer / Fragrance

0.8 FL OZ (24mL)

82999-001-08